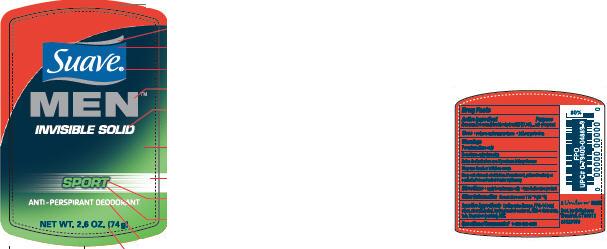 DRUG LABEL: Suave Men Sport
NDC: 64942-1077 | Form: STICK
Manufacturer: Conopco Inc. d/b/a Unilever
Category: otc | Type: HUMAN OTC DRUG LABEL
Date: 20100511

ACTIVE INGREDIENTS: Aluminum Zirconium Tetrachlorohydrex GLY 17.8 g/100 g

PDP and Drug facts box text for Suave Men Sport Antiperspirant and Deodorant

Active ingredient Purpose

Aluminum Zirconium Tetrachlorohydrex GLY (17.8%).......................................antiperspirant

WARNINGS

For external use only

Do not use on broken skin

Ask a doctor before use if you have kidney disease

Stop use if rash or irritation occurs

Keep out of reach of children. If swallowed, get medical help or contact a Poison Control Center right away.

Inactive Ingredients
Cyclopentasiloxane, PPG-14 Butyl Ether, Stearyl Alcohol, Hydrogenated Castor Oil, PEG-8 Distearate, Talc, Fragrance (Parfum), BHT.

Questions?
Call 1-800-782-8301

PACKAGE LABEL

PDP 2.6 oz